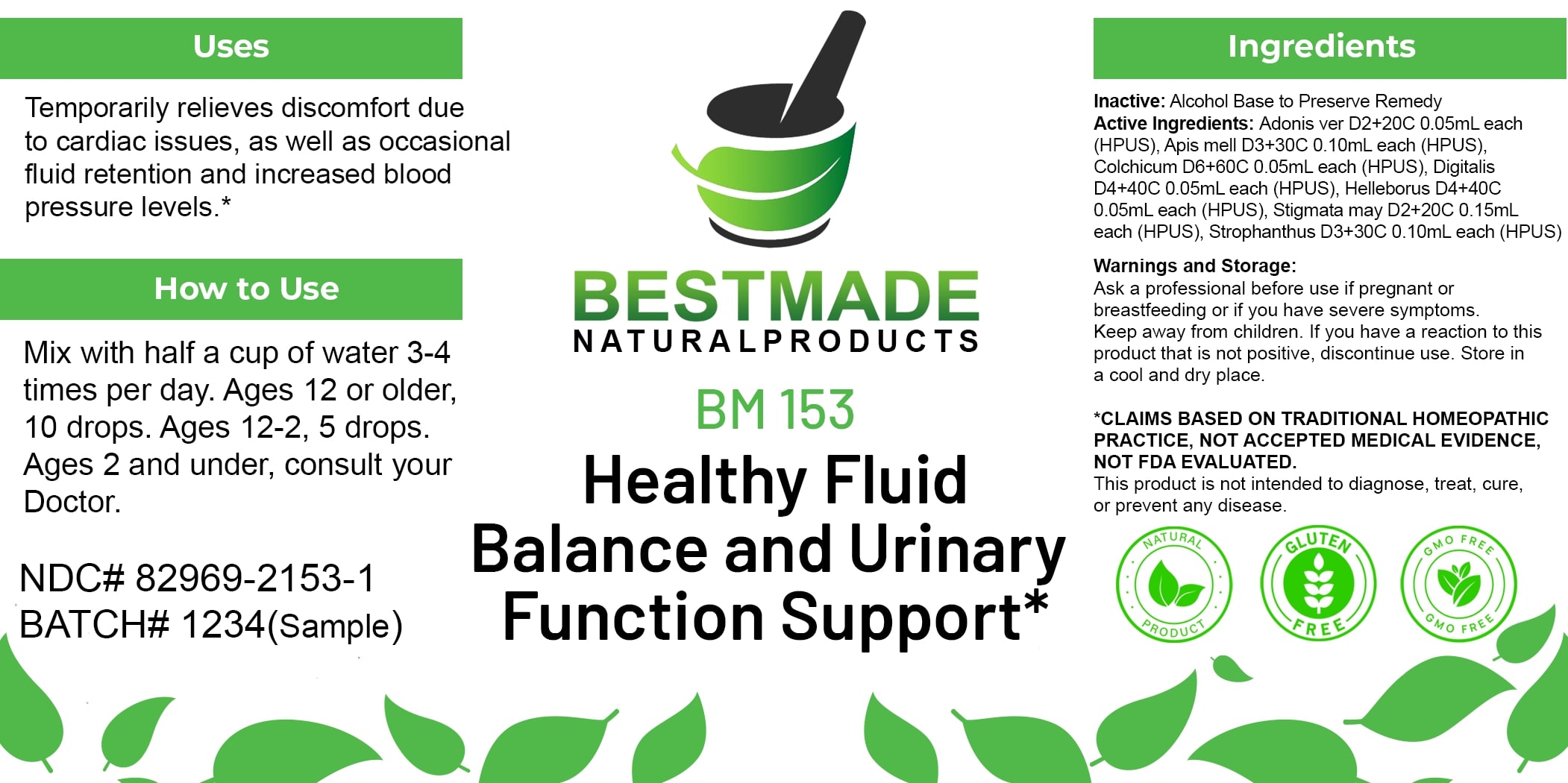 DRUG LABEL: Bestmade Natural Products BM153
NDC: 82969-2153 | Form: LIQUID
Manufacturer: Bestmade Natural Products
Category: homeopathic | Type: HUMAN OTC DRUG LABEL
Date: 20250218

ACTIVE INGREDIENTS: APIS MELLIFERA 30 [hp_C]/30 [hp_C]; HELLEBORUS NIGER ROOT 30 [hp_C]/30 [hp_C]; ADONIS VERNALIS WHOLE 30 [hp_C]/30 [hp_C]; CORN SILK 30 [hp_C]/30 [hp_C]; DIGITALIS 30 [hp_C]/30 [hp_C]; COLCHICUM AUTUMNALE BULB 30 [hp_C]/30 [hp_C]; STROPHANTHUS HISPIDUS SEED 30 [hp_C]/30 [hp_C]
INACTIVE INGREDIENTS: ALCOHOL 30 [hp_C]/30 [hp_C]

BM153

DOSAGE AND ADMINISTRATION

How to Use

Mix with half a cup of water 3-4 times per day. Ages 12 or older, 10 drops. Ages 12-2, 5 drops. Ages 2 and under, consult your Doctor.

INACTIVE INGREDIENT

Ingredients

Inactive: Alcohol Base to Preserve Remedy

ACTIVE INGREDIENT

Active Ingredients: Adonis ver D2+20C 0.05ml each (HPUS), Apis mell D3+30C 0.10mL each (HPUS), Colchicum D6+60C 0.05mL each (HPUS), Digitalis D4+40C 0.05mL each (HPUS), Helleborus D4+40C 0.05mL each (HPUS), Stigmata may D2+20C 0.15mL each (HPUS), Strophanthus D3+30C 0.10mL each (HPUS).

Uses

Temporarily relieves discomfort due to cardiac issues, as well as occasional fluid retention and increased blood pressure levels.*

*CLAIMS BASED ON TRADITIONAL HOMEOPATHIC PRACTICE, NOT ACCEPTED MEDICAL EVIDENCE. NOT FDA EVALUATED.

This product is not intended to diagnose, treat, cure, or prevent any disease.

Uses

Temporarily relieves discomfort due to cardiac issues, as well as occasional fluid retention and increased blood pressure levels.*

*CLAIMS BASED ON TRADITIONAL HOMEOPATHIC PRACTICE, NOT ACCEPTED MEDICAL EVIDENCE. NOT FDA EVALUATED.

This product is not intended to diagnose, treat, cure, or prevent any disease.

KEEP OUT OF REACH OF CHILDREN

Warnings and Storage:

Ask a professional before use if pregnant or breastfeeding or if you have severe symptoms. Keep away from children. If you have a reaction to this product that is not positive, discontinue use. Store in a cool and dry place.

Warnings and Storage:

Ask a professional before use if pregnant or breastfeeding or if you have severe symptoms. Keep away from children. If you have a reaction to this product that is not positive, discontinue use. Store in a cool and dry place.

*CLAIMS BASED ON TRADITIONAL HOMEOPATHIC PRACTICE, NOT ACCEPTED MEDICAL EVIDENCE. NOT FDA EVALUATED.

This product is not intended to diagnose, treat, cure, or prevent any disease.

Entire package label